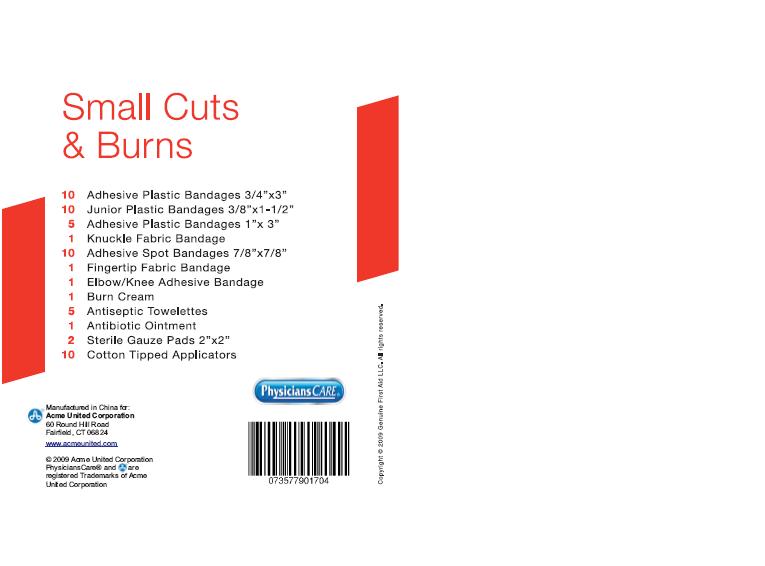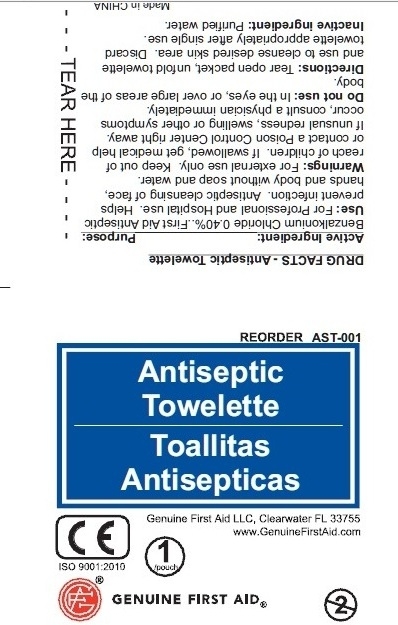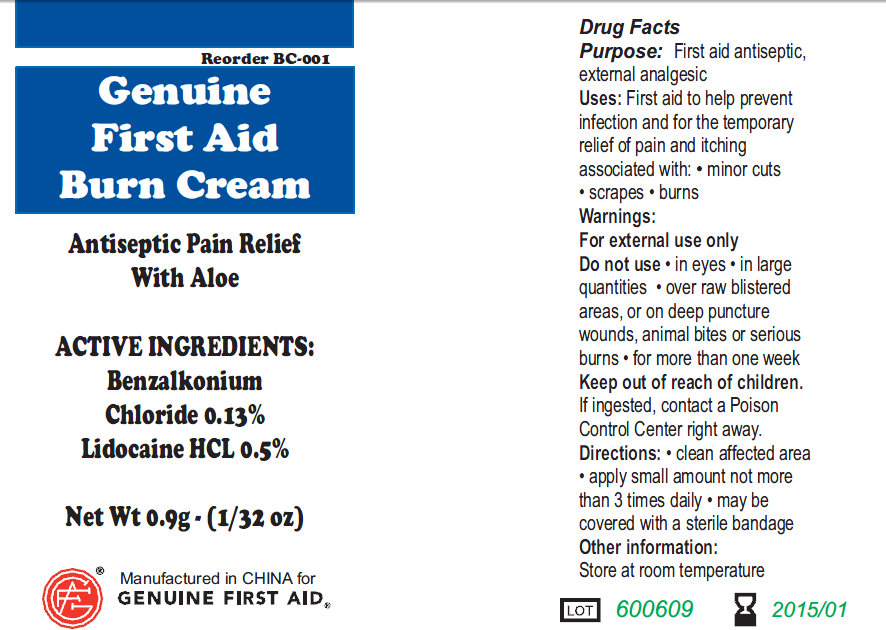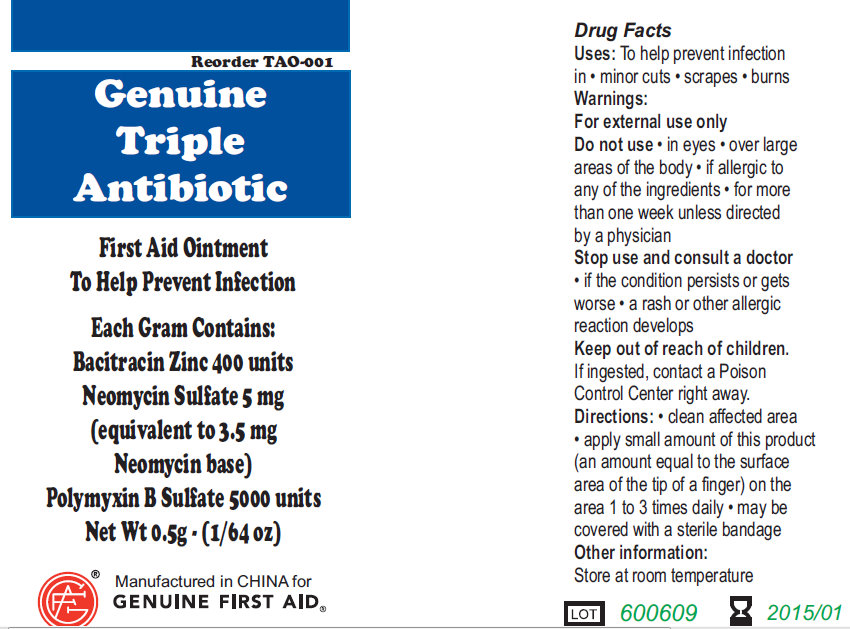 DRUG LABEL: ACME Small Cuts and Burns
NDC: 0924-1805 | Form: KIT | Route: TOPICAL
Manufacturer: Acme United Corp.
Category: otc | Type: HUMAN OTC DRUG LABEL
Date: 20100614

ACTIVE INGREDIENTS: BENZALKONIUM CHLORIDE 0.13 g/100 g; LIDOCAINE 0.5 g/100 g; BENZALKONIUM CHLORIDE 0.40 mL/100 mL; BACITRACIN ZINC 400 [iU]/1 g; NEOMYCIN SULFATE 5 mg/1 g; POLYMYXIN B SULFATE 5000 [iU]/1 g
INACTIVE INGREDIENTS: WATER

ACME Small Cuts and Burns

Active Ingredients:

Benzalkonium Chloride 0.13%

Lidocaine HCL 0.5%

Purpose: First aid antiseptic, external analgesic
Uses: First aid to help prevent infection and for
the temporary relief of pain and itching associated with:
minor cuts, scrapes, burns

WARNINGS

Warning: For external use only.

Do not use: in eyes, in large quantities, over raw blistered areas,

or on deep puncture wounds, animal bites or serious burns, for more than one week

Keep out of reach of children.

If ingested, contact a Poison Control Center right away.

DOSAGE AND ADMINISTRATION

Directions: Clean affected area, Apply small amount not more than 3 times daily.
May be covered with a sterile bandage.

Other Information:
Store at room temperature

DESCRIPTION

LOT/EXP: Made in CHINA
20130301

PACKAGE LABEL

Genuine First Aid Burn Cream
Antiseptic Pain Relief With Aloe
Net Wt 0.9g (1/32 oz)
Manufactured in CHINA for
Genuine First Aid.

Active Ingredient: Purpose

Benzalkonium Chloride 0.40%... First Aid Antiseptic

PURPOSE

Use: For Professional and Hospital use. Helps
prevent infection. Antiseptic cleansing of face,
hands and body without soap and water.

WARNINGS

Warning: For external use only.

Keep out of reach of children: If swallowed, get medical help
or contact a Poison Control Center right away.

Stop use if unusual redness, swelling or other symptoms occur.

Consult a physician immediately.

Do not use in the eyes or over large areas of
the body.

WHEN USING

Directions: Tear open packet, unfold towelette
and use to cleanse desired skin area. Discard
towelette appropriately after single use.

Inactive Ingredient: Purified water

DESCRIPTION

LOT/EXP: Made in CHINA
20130301

PACKAGE LABEL

Antiseptic Towelette
Genuine First Aid LLC, Clearwater FL 33755
www.GenuineFirstAid.com
GENUINE FIRST AID

Active Ingredient: .........Bacitracin Zinc 400 units
Neomycin Sulfate 5mg (equivalent to 3.5 mg Neomycin base)
Polymyxin B Sulfate 5000 units

PURPOSE

Uses: To help prevent infection in:
minor cuts; scrapes; burns

Warnings:
For external use only.

Do not use: in eyes; over large areas of the body;
If allergic to any of the ingredients; for more than one week unless directed by a physician.

Stop use and consult a doctor:

if the condition persists or gets worse; a rash or other allergic reaction develops

Keep out of reach of children.
If ingested, contact a Poison
Control Center right away.

WHEN USING

Directions: clean affected area; apply small amount of this product (an amount equal to the surface area of the tip of a finger) on the area 1 to 3 times daily; may be covered with a sterile bandage

Other information:
Store at room temperature.

PACKAGE LABEL

Genuine Triple Antibiotic
First Aid Ointment
To Help Prevent Infection
Each Gram Contains:
Bacitracin Zinc 400 units
Neomycin Sulfate 5 mg
(equivalent to 3.5 mg
Neomycin base)
Polymyxin B Sulfate 5000 units
Net Wt. 0.5g ; (1/64 oz)
Manufactured in CHINA for
GENUINE FIRST AID.

PACKAGE LABEL

Small Cuts and Burns

10 Adhesive Plastic Bandages 3/4"x3"
10 Junior Plastic Bandages 3/8"x1-1/2"
5 Adhesive Plastic Bandages 1"x3"
1 Knuckle Fabric Bandage
10 Adhesive Spot Bandages 7/8"x7/8"
1 Fingertip Fabric Bandage
1 Elbow/Knee Adhesive Bandage
1 Burn Cream
5 Antiseptic Towelettes
1 Antibiotic Ointment
2 Sterile Gauge Pads 2"x2"
10 Cotton Tipped Applicators
Manufactured in China for:
Acme United Corporation
60 Round Hill Road
Fairfield, CT 06824
www.acmeunited.com
© 2009 Acme United Corporation
PhysiciansCare® and are
registered Trademarks of Acme
United Corporation
Physicians CARE
Copyright C 2009 Genuine First Aid LLC. All rights reserved.